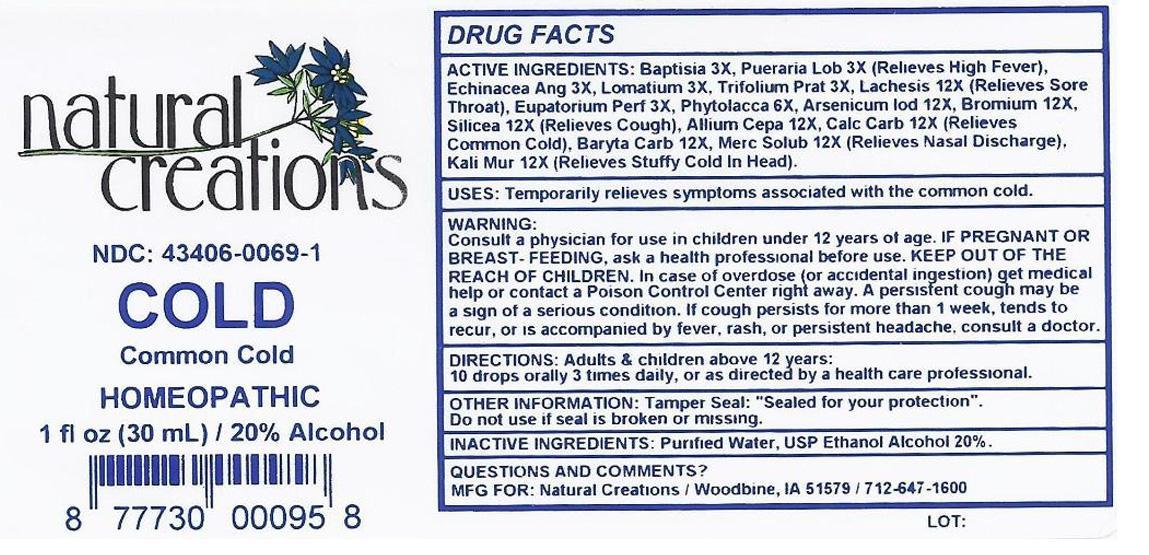 DRUG LABEL: COLD
NDC: 43406-0069 | Form: LIQUID
Manufacturer: Natural Creations, Inc.
Category: homeopathic | Type: HUMAN OTC DRUG LABEL
Date: 20130128

ACTIVE INGREDIENTS: BAPTISIA TINCTORIA ROOT 3 [hp_X]/1 mL; ECHINACEA ANGUSTIFOLIA 3 [hp_X]/1 mL; EUPATORIUM PERFOLIATUM FLOWERING TOP 3 [hp_X]/1 mL; PUERARIA MONTANA VAR. LOBATA ROOT 3 [hp_X]/1 mL; TRIFOLIUM PRATENSE FLOWER 3 [hp_X]/1 mL; PHYTOLACCA AMERICANA ROOT 6 [hp_X]/1 mL; ONION 12 [hp_X]/1 mL; ARSENIC TRIIODIDE 12 [hp_X]/1 mL; BARIUM CARBONATE 12 [hp_X]/1 mL; BROMINE 12 [hp_X]/1 mL; OYSTER SHELL CALCIUM CARBONATE, CRUDE 12 [hp_X]/1 mL; POTASSIUM CHLORIDE 12 [hp_X]/1 mL; LACHESIS MUTA VENOM 12 [hp_X]/1 mL; MERCURIUS SOLUBILIS 12 [hp_X]/1 mL; SILICON DIOXIDE 12 [hp_X]/1 mL
INACTIVE INGREDIENTS: WATER; ALCOHOL

ACTIVE INGREDIENT

ACTIVE INGREDIENTS: Baptisia Tinctoria 3X, Echinacea Angustifolia 3X, Eupatorium Perfoliatum 3X, Lomatium Dissectum 3X, Pueraria Lobata 3X, Trifolium Pratense 3X, Phytolacca Decandra 6X, Allium Cepa 12X, Arsenicum Iodatum 12X, Baryta Carbinica 12 X, Bromium 12X, Calcarea Carbonica 12X, Kali Muriaticum 12X, Lachesis Mutus 12X, Mercuris Solubilis 12X, Silicea 12X

PURPOSE

USES: Temporarily relievews symptoms associated with with the common cold.

KEEP OUT OF REACH OF CHILDREN

KEEP OUT OF THE REACH OF CHILDREN. In case of overdose (or accidential ingestion) get medical help or contact a Poison Control Center.

INDICATIONS AND USAGE

USES: Temporarily relieves symptoms associated with the common cold.

WARNING:

Consult a physician for use in children under 12 years of age. IF PREGNANT OR BREAST-FEEDING, as a health care professional before use. KEEP OUT OF THE REACH OF CHILDREN. In case of overdose (or accidential ingestion) get medical help or cantact a Poison control Center right away.

DOSAGE AND ADMINISTRATION

DIRECTIONS: Adults and children above 12 years: 10 drops orally 3 times daily, or as directed by a health care prosessional.

INACTIVE INGRIDENTS: Purified Warter, USP Ethanol Alcohol 20%

PACKAGE LABEL

NDC: 43406-0069-1

COLD

Copmmon Cold

HOMEOPATHIC

1 fl oz (30 mL) / 20% Alcohol

8 77730 00095 8